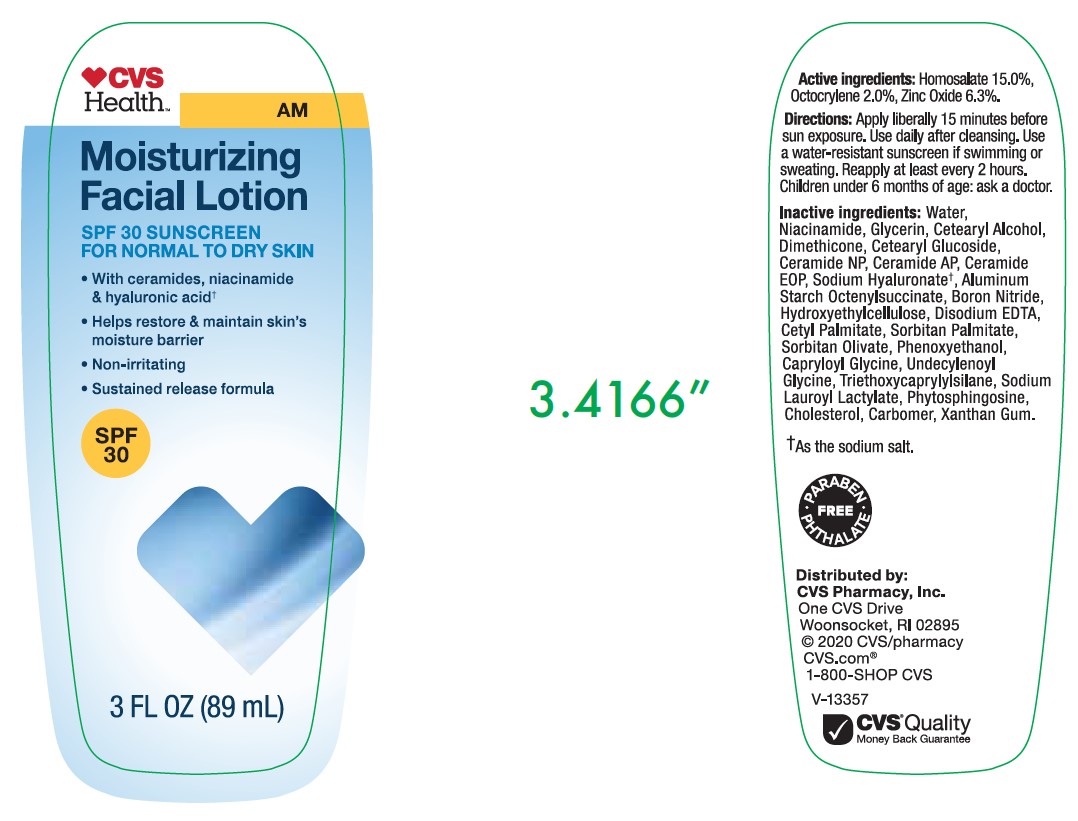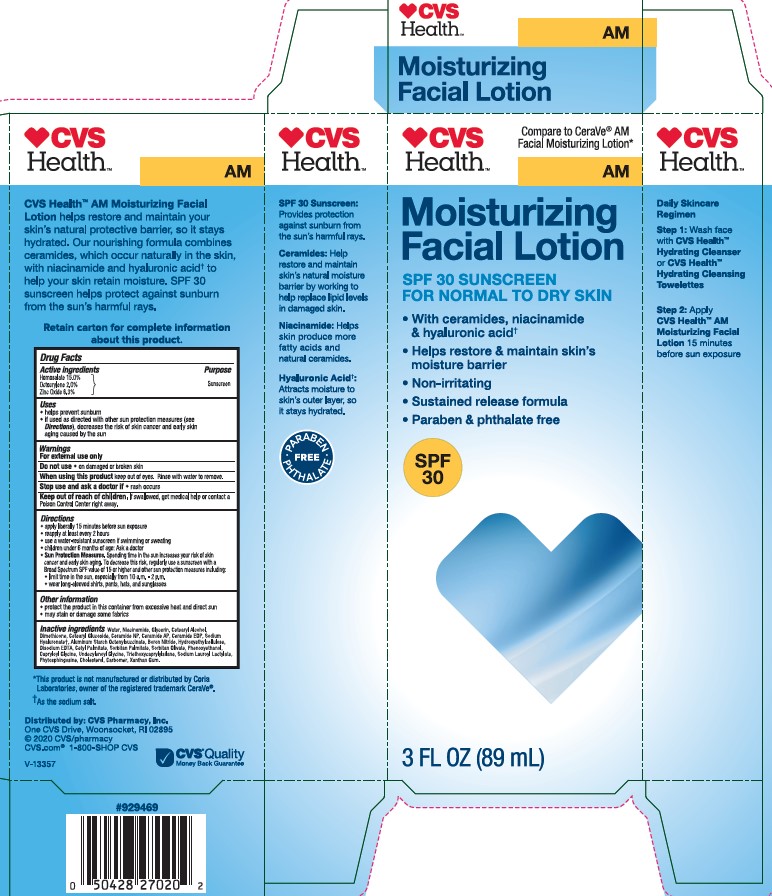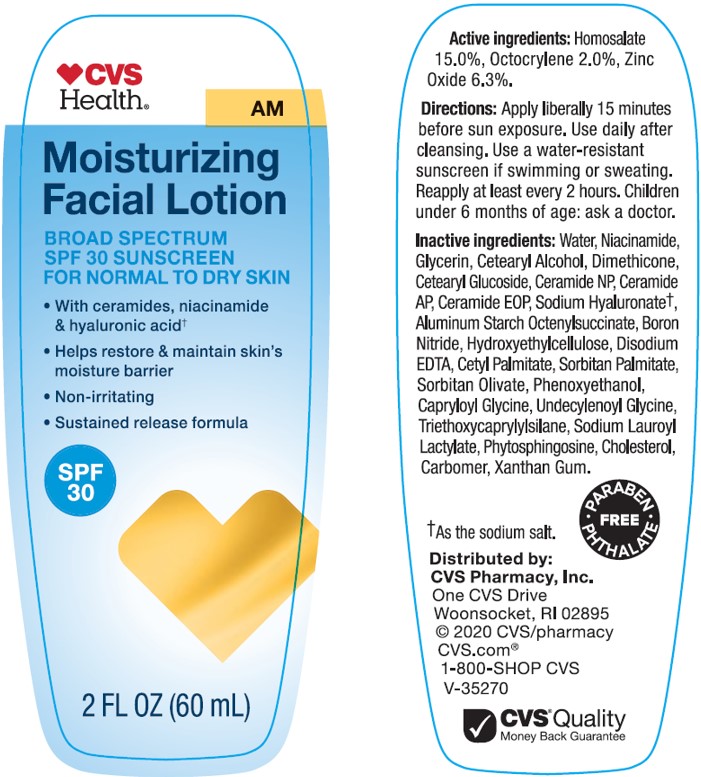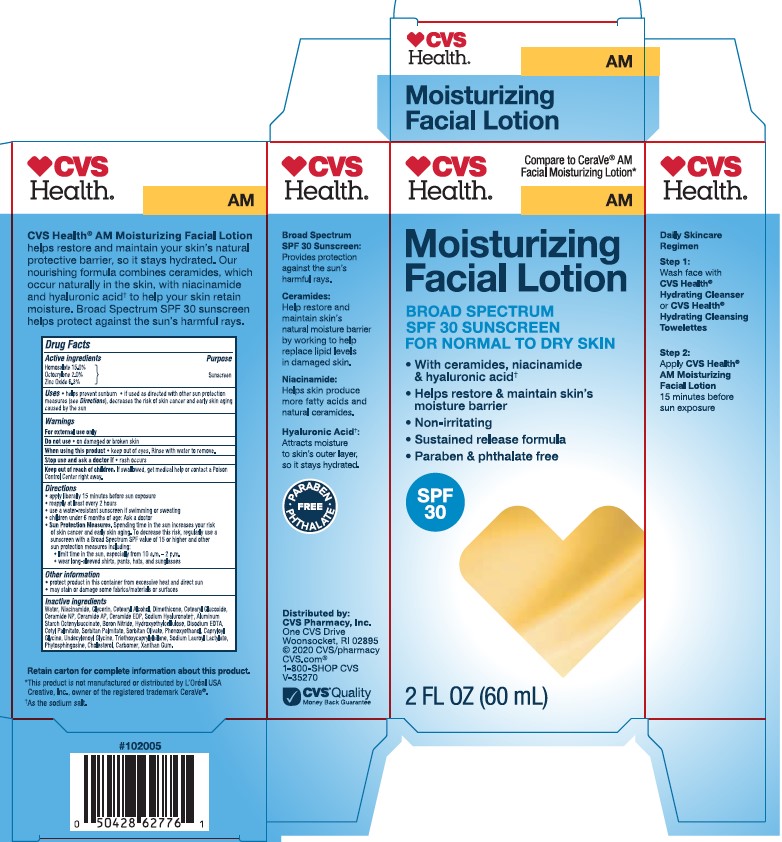 DRUG LABEL: CVS Health AM Moisturizing Facial Broad Spectrum SPF 30 Sunscreen
NDC: 51316-042 | Form: LOTION
Manufacturer: CVS PHARMACY
Category: otc | Type: HUMAN OTC DRUG LABEL
Date: 20241017

ACTIVE INGREDIENTS: HOMOSALATE 150 mg/1 mL; ZINC OXIDE 63 mg/1 mL; OCTOCRYLENE 20 mg/1 mL
INACTIVE INGREDIENTS: CERAMIDE NP; CETEARYL GLUCOSIDE; SODIUM LAUROYL LACTYLATE; ALUMINUM STARCH OCTENYLSUCCINATE; CERAMIDE AP; CAPRYLOYL GLYCINE; CETYL PALMITATE; BORON NITRIDE; CHOLESTEROL; HEXAMETHYLDISILOXANE; HYDROXYETHYL CELLULOSE (2000 CPS AT 1%); PHYTOSPHINGOSINE; HYALURONATE SODIUM; SORBITAN MONOPALMITATE; TRIETHOXYCAPRYLYLSILANE; UNDECYLENOYL GLYCINE; NIACINAMIDE; SORBITAN OLIVATE; XANTHAN GUM; POLYACRYLIC ACID (8000 MW); WATER; GLYCERIN; EDETATE DISODIUM; CETOSTEARYL ALCOHOL; PHENOXYETHANOL

CVS Health AM Moisturizing Facial Lotion Broad Spectrum SPF 30 Sunscreen

Active ingredients

Homosalate15.0%, Octocrylene 2.0%, Zinc Oxide 6.3%

Purpose

Sunscreen

Uses

- helps prevent sunburn
- if used as directed with other sun protection measures (see Directions), decreases the risk of skin cancer and early skin aging caused by the sun

Warnings

For external use only

Do not use

• on damaged or broken skin.

When using this product

• keep out of eyes. Rinse with water to remove.

Stop use and ask a doctor if

• rash occurs.

Keep out of reach of children.

If swallowed, get medical help or contact a Poison Control Center right away.

Directions

- apply liberally 15 minutes before sun exposure
- use a water resistant sunscreen if swimming or sweating
- reapply at least every 2 hours
- children under 6 months of age: Ask a doctor
- Sun Protection Measures. Spending time in the sun increases your risk of skin cancer and early skin aging. To decrease this risk, regularly use a sunscreen with a Broad Spectrum SPF value of 15 or higher and other sun protection measures including:

• limit time in the sun, especially from 10 a.m. - 2 p.m.

• wear long-sleeved shirts, pants, hats, and sunglasses

Other information

- protect the product in this container from excessive heat and direct sun
- may stain or damage some fabrics, materials or surfaces

Inactive ingredients

Water, Niacinamide, Glycerin, Cetearyl Alcohol, Dimethicone, Cetearyl Glucoside, Ceramide NP, Ceramide AP, Ceramide EOP, Sodium Hyaluronate, Aluminum Starch Octenylsuccinate, Boron Nitride, Hydroxyethylcellulose, Disodium EDTA, Cetyl Palmitate, Sorbitan Palmitate, Sorbitan Olivate, Phenoxyethanol, Capryloyl Glycine, Undecylenoyl Glycine, Triethoxycaprylylsilane, Sodium Lauroyl Lactylate, Phytosphingosine, Cholesterol, Carbomer, Xanthan Gum.